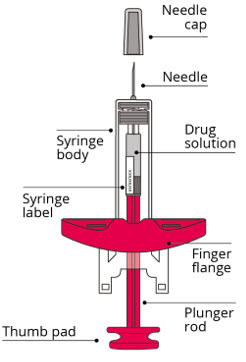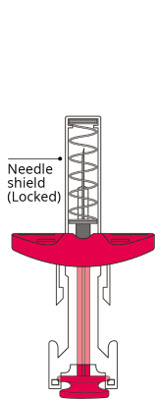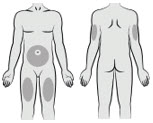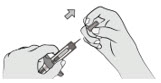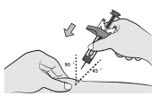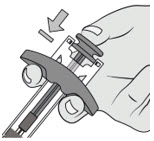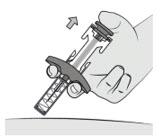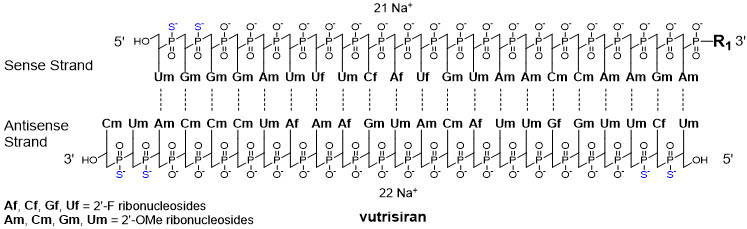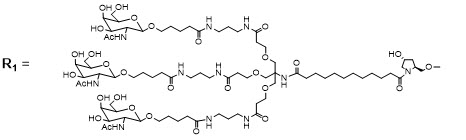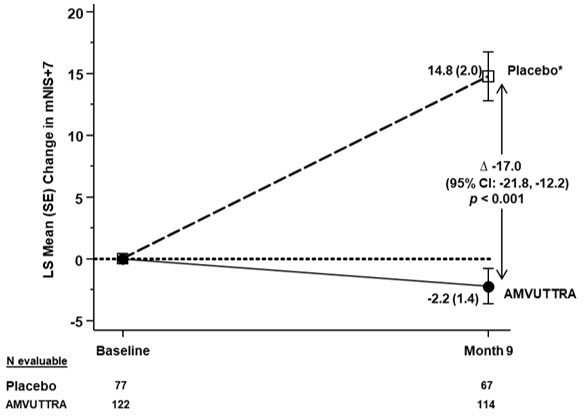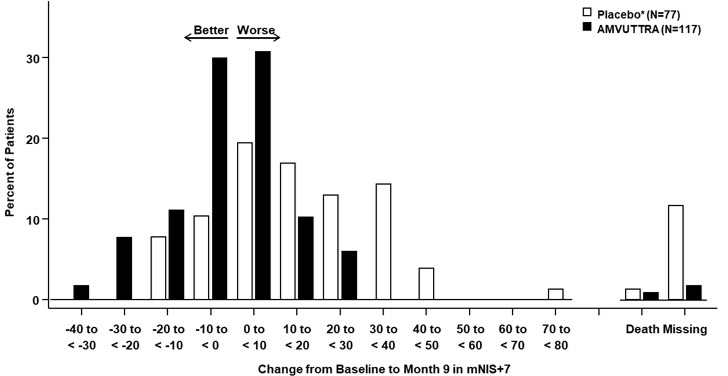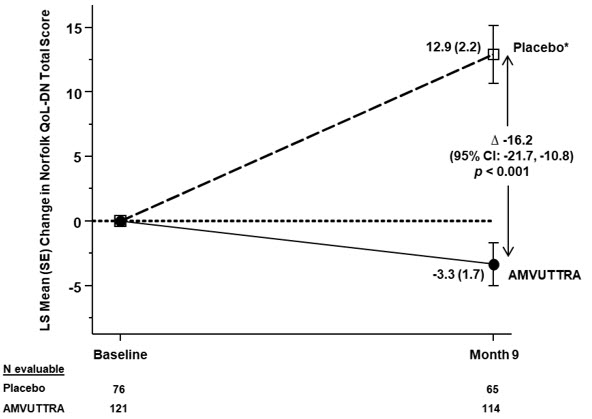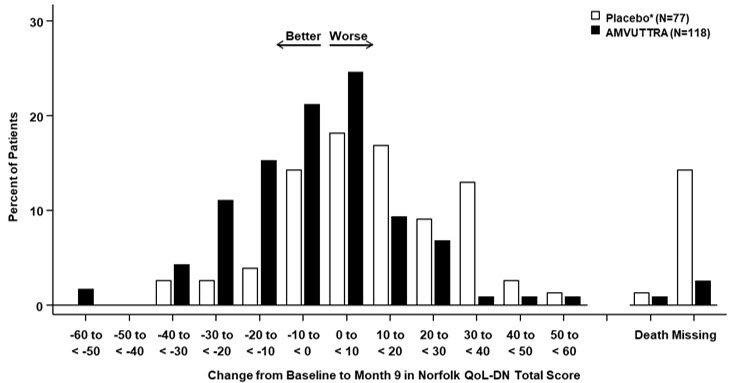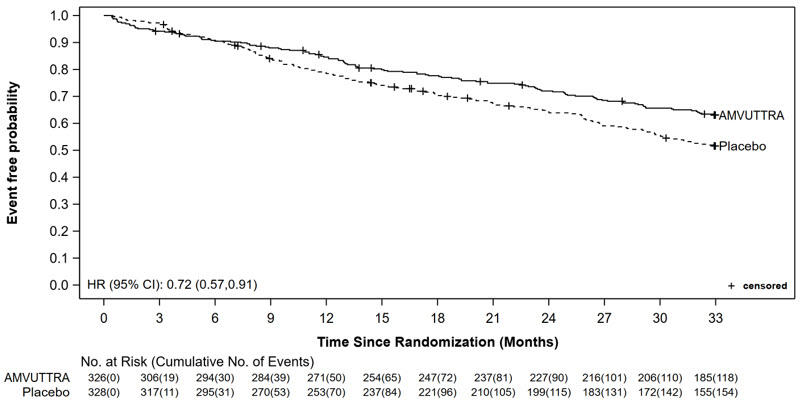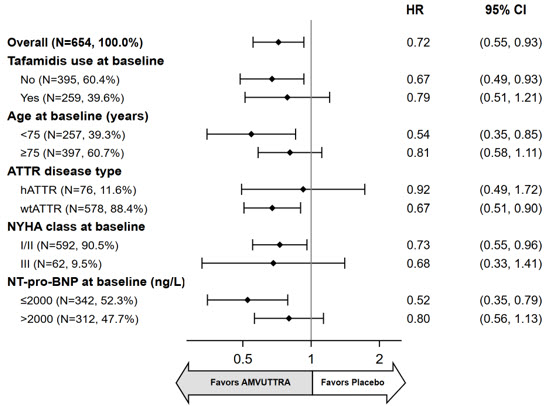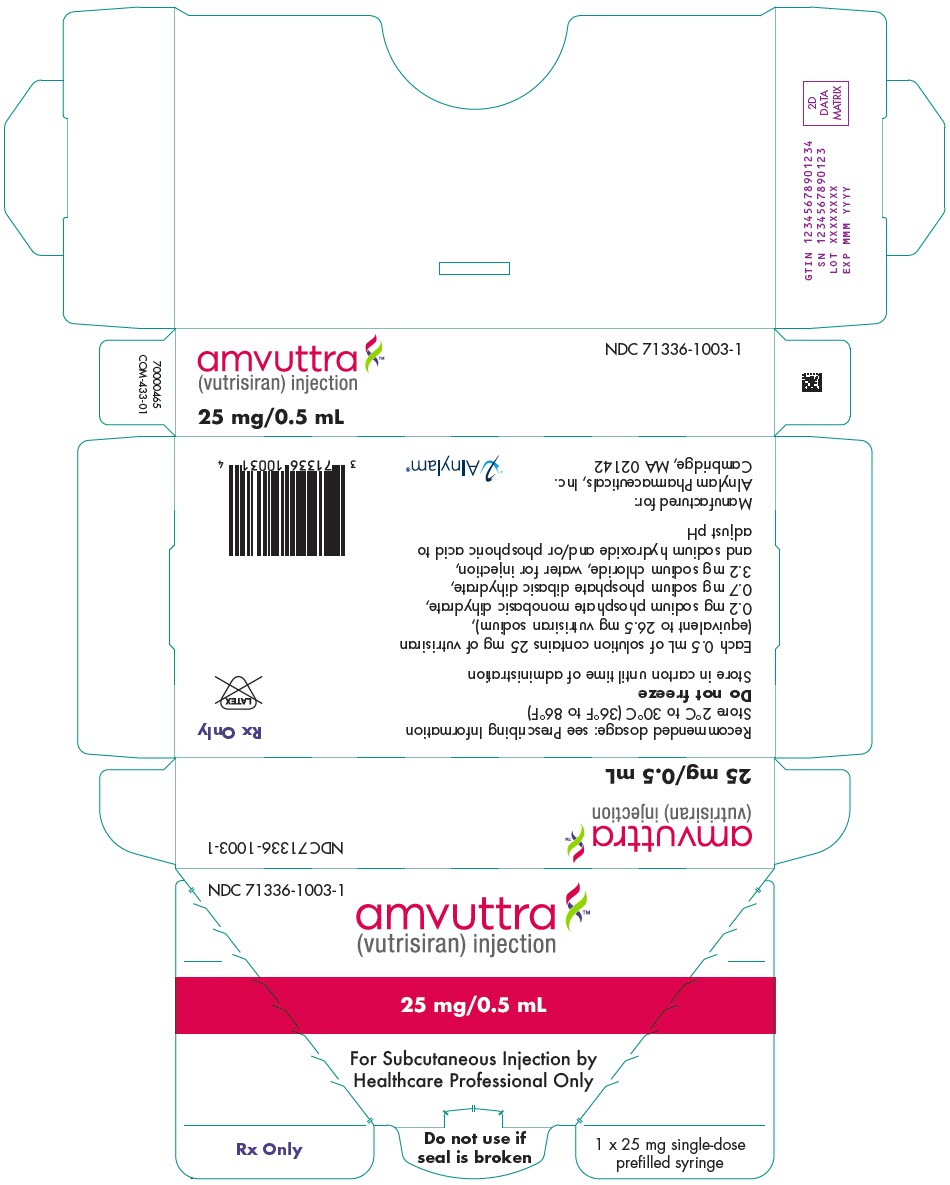 DRUG LABEL: AMVUTTRA
NDC: 71336-1003 | Form: INJECTION
Manufacturer: Alnylam Pharmaceuticals, Inc.
Category: prescription | Type: HUMAN PRESCRIPTION DRUG LABEL
Date: 20251106

ACTIVE INGREDIENTS: VUTRISIRAN SODIUM 25 mg/0.5 mL
INACTIVE INGREDIENTS: WATER; Sodium hydroxide; Phosphoric acid; SODIUM PHOSPHATE, MONOBASIC, DIHYDRATE; SODIUM PHOSPHATE, DIBASIC, DIHYDRATE; Sodium chloride

HIGHLIGHTS OF PRESCRIBING INFORMATION

These highlights do not include all the information needed to use AMVUTTRA® safely and effectively. See full prescribing information for AMVUTTRA.
AMVUTTRA (vutrisiran) injection, for subcutaneous use
Initial U.S. Approval: 2022

RECENT MAJOR CHANGES

Indication and Usage (1) | 3/2025

1 INDICATIONS AND USAGE

AMVUTTRA is a transthyretin-directed small interfering RNA indicated for the treatment of:

- the polyneuropathy of hereditary transthyretin-mediated amyloidosis in adults (1.1)
- the cardiomyopathy of wild-type or hereditary transthyretin-mediated amyloidosis in adults to reduce cardiovascular mortality, cardiovascular hospitalizations and urgent heart failure visits (1.2)

2 DOSAGE AND ADMINISTRATION

- The recommended dosage of AMVUTTRA is 25 mg administered by subcutaneous injection once every 3 months. (2.1)
- AMVUTTRA is for subcutaneous use only and should be administered by a healthcare professional. (2.2)

3 DOSAGE FORMS AND STRENGTHS

Injection: 25 mg/0.5 mL in a single-dose prefilled syringe. (3)

4 CONTRAINDICATIONS

None. (4)

5 WARNINGS AND PRECAUTIONS

Reduced serum vitamin A levels and recommended supplementation: Supplement with the recommended daily allowance of vitamin A. Refer to an ophthalmologist if ocular symptoms suggestive of vitamin A deficiency occur. (5.1)

6 ADVERSE REACTIONS

The most common adverse reactions (≥5%) were pain in extremity, arthralgia, dyspnea, and vitamin A decreased. (6.1)

To report SUSPECTED ADVERSE REACTIONS, contact Alnylam Pharmaceuticals at 1-877-256-9526 or FDA at 1-800-FDA-1088 or www.fda.gov/medwatch.

FULL PRESCRIBING INFORMATION

1 INDICATIONS AND USAGE

1.1 Polyneuropathy of Hereditary Transthyretin-mediated Amyloidosis

AMVUTTRA is indicated for the treatment of the polyneuropathy of hereditary transthyretin-mediated amyloidosis (hATTR-PN) in adults.

1.2 Cardiomyopathy of Wild-type or Hereditary Transthyretin-mediated Amyloidosis

AMVUTTRA is indicated for the treatment of the cardiomyopathy of wild-type or hereditary transthyretin-mediated amyloidosis (ATTR-CM) in adults to reduce cardiovascular mortality, cardiovascular hospitalizations and urgent heart failure visits.

2 DOSAGE AND ADMINISTRATION

2.1 Recommended Dosage

The recommended dosage of AMVUTTRA is 25 mg administered by subcutaneous injection once every 3 months [see Dosage and Administration (2.2)].

Missed Dose

If a dose is missed, administer AMVUTTRA as soon as possible. Resume dosing every 3 months from the most recently administered dose.

2.2 Administration Instructions

AMVUTTRA is for subcutaneous use only and should be administered by a healthcare professional.

Syringe Appearance Before and After Use

Before Use

After Use

Preparation and Administration

1. Prepare the syringe
  If stored cold, allow the syringe to warm to room temperature for 30 minutes prior to use.
  Remove the syringe from the packaging by gripping the syringe body.
  Do not touch the plunger rod until ready to inject.
  Visually inspect the drug solution for discoloration and particulate matter prior to administration. AMVUTTRA is a sterile, preservative-free, clear, colorless-to-yellow solution. Do not use if it contains particulate matter or if it is cloudy or discolored.
  Check the following:
  - Syringe is not damaged, such as cracked or leaking
  - Needle cap is attached to the syringe
  - Expiration date on syringe label
  Do not use the syringe if any issues are found while checking the syringe.

2. Choose and prepare the injection site
  Choose an injection site from the following areas: the abdomen, thighs, or upper arms.
  Avoid the following:
  - 5-cm area around the navel
  - Scar tissue or areas that are reddened, inflamed, or swollen
  Clean the chosen injection site.

3. Prepare the syringe for injection
  Hold the syringe body with one hand. Pull the needle cap straight off with other hand and dispose of needle cap immediately. It is normal to see a drop of liquid at the tip of the needle.
  Do not touch the needle or let it touch any surface.
  Do not recap the syringe.
  Do not use the syringe if it is dropped.

4. Perform the injection
  Pinch the cleaned skin.
  Fully insert the needle into the pinched skin at a 45°-90° angle.

Inject all of the medication.
  Push the plunger rod as far as it will go to administer the dose and activate the needle shield.

Release the plunger rod to allow the needle shield to cover the needle.
  Do not block plunger rod movement.

5. Dispose of the syringe
  Immediately dispose of the used syringe into a sharps container.

3 DOSAGE FORMS AND STRENGTHS

Injection: 25 mg/0.5 mL of vutrisiran as a clear, colorless-to-yellow solution in a single-dose prefilled syringe.

4 CONTRAINDICATIONS

None.

5 WARNINGS AND PRECAUTIONS

5.1 Reduced Serum Vitamin A Levels and Recommended Supplementation

AMVUTTRA treatment leads to a decrease in serum vitamin A levels [see Adverse Reactions (6.1) and Clinical Pharmacology (12.2)].

Supplementation at the recommended daily allowance of vitamin A is advised for patients taking AMVUTTRA. Higher doses than the recommended daily allowance of vitamin A should not be given to try to achieve normal serum vitamin A levels during treatment with AMVUTTRA, as serum vitamin A levels do not reflect the total vitamin A in the body.

Patients should be referred to an ophthalmologist if they develop ocular symptoms suggestive of vitamin A deficiency (e.g., night blindness).

6 ADVERSE REACTIONS

The following clinically significant adverse reactions are discussed in greater detail in other sections of the labeling:

- Reduced Serum Vitamin A Levels and Recommended Supplementation [see Warnings and Precautions (5.1)]

6.1 Clinical Trials Experience

Because clinical trials are conducted under widely varying conditions, adverse reaction rates observed in the clinical trials of AMVUTTRA cannot be directly compared to rates in the clinical trials of another drug and may not reflect the rates observed in practice.

Two Phase 3 randomized, multi-center studies evaluated the safety of AMVUTTRA in 448 transthyretin-mediated amyloidosis (ATTR) patients, including 122 patients with hATTR-PN (HELIOS-A) and 326 patients with ATTR-CM (HELIOS-B) [see Clinical Studies (14)]. In both studies, patients were instructed to take the recommended daily allowance of vitamin A [see Warnings and Precautions (5.1)].

Polyneuropathy of Hereditary Transthyretin-mediated Amyloidosis

In HELIOS-A, 118 patients received at least 18 months of treatment. The mean duration of treatment was 18.8 months (range: 1.7 to 19.4 months). The median patient age at baseline was 60 years and 65% of the patients were male. Seventy percent of AMVUTTRA-treated patients were Caucasian, 17% were Asian, 3% were Black, and 9% were reported as Other. Forty-four percent of patients had the Val30Met mutation in the transthyretin gene; the remaining patients had one of 21 other mutations. At baseline, 70% of patients were in Stage 1 of the disease and 30% were in Stage 2.

The most common adverse reactions (at least 5%) were pain in extremity, arthralgia, dyspnea, and vitamin A decreased (see Table 1).

Seventy-four percent of patients treated with AMVUTTRA had normal vitamin A levels at baseline, and 98% of those with a normal baseline developed low vitamin A levels. In some cases, the decreased vitamin A level was reported as an adverse reaction (see Table 1).

Table 1: Adverse Reactions Reported in at least 5% of Patients Treated with AMVUTTRA in HELIOS-A
Adverse Reaction | AMVUTTRA N=122 %
Pain in extremity | 15
Arthralgia [Comprised of several similar terms] | 11
Dyspnea | 7
Vitamin A decreased [Percentage only reflects those reported as an adverse reaction] | 7

In HELIOS-A, two serious adverse reactions of atrioventricular (AV) heart block (1.6%) occurred in patients treated with AMVUTTRA, including one case of complete AV block.

Injection site reactions were reported in 5 (4%) patients treated with AMVUTTRA. Reported symptoms included bruising, erythema, pain, pruritus, and warmth. Injection site reactions were mild and transient.

Cardiomyopathy of Wild-type or Hereditary Transthyretin-mediated Amyloidosis

In HELIOS-B, safety was evaluated in 654 patients with ATTR-CM, which included 257 patients treated with AMVUTTRA for ≥30 months, and 77 patients treated with AMVUTTRA for ≥36 months [see Clinical Studies (14)]. No new safety issues were identified. Eighty-two percent of patients treated with AMVUTTRA had normal vitamin A levels at baseline, and 80% of those with a normal baseline developed low vitamin A levels.

8 USE IN SPECIFIC POPULATIONS

8.1 Pregnancy

Risk Summary

There are no available data on AMVUTTRA use in pregnant women to inform a drug-associated risk of adverse developmental outcomes. AMVUTTRA treatment leads to a decrease in serum vitamin A levels, and vitamin A supplementation is advised for patients taking AMVUTTRA. Vitamin A is essential for normal embryofetal development; however, excessive levels of vitamin A are associated with adverse developmental effects. The effects on the fetus of a reduction in maternal serum TTR caused by AMVUTTRA and of vitamin A supplementation are unknown [see Warnings and Precautions (5.1) and Clinical Pharmacology (12.2)].

In animal studies, subcutaneous administration of vutrisiran to pregnant rats resulted in developmental toxicity (reduced fetal body weight and embryofetal mortality) at doses associated with maternal toxicity (see Data).

In the U.S. general population, the estimated background risk of major birth defects and miscarriage in clinically recognized pregnancies is 2% to 4% and 15% to 20%, respectively. The background risk of major birth defects and miscarriage for the indicated population is unknown.

Data

Animal Data

Subcutaneous administration of vutrisiran (0, 3, 10, or 30 mg/kg/day) to pregnant rats during the period of organogenesis resulted in embryofetal mortality at the high dose and reduced fetal body weight at the mid and high doses, which were associated with maternal toxicity.

Subcutaneous administration of vutrisiran (0, 3, 10, or 30 mg/kg/day) to pregnant rabbits resulted in no adverse effects on embryofetal development.

Subcutaneous administration of vutrisiran (0, 5, 10, or 20 mg/kg) to pregnant rats every 6 days throughout pregnancy and lactation resulted in no adverse developmental effects on the offspring.

8.2 Lactation

Risk Summary

There is no information regarding the presence of vutrisiran in human milk, the effects on the breastfed infant, or the effects on milk production. The developmental and health benefits of breastfeeding should be considered along with the mother's clinical need for AMVUTTRA and any potential adverse effects on the breastfed infant from AMVUTTRA or from the underlying maternal condition.

8.4 Pediatric Use

Safety and effectiveness in pediatric patients have not been established.

8.5 Geriatric Use

No dose adjustment is required in patients ≥65 years of age [see Clinical Pharmacology (12.3)]. In HELIOS-A, a total of 46 (38%) patients ≥65 years of age, including 7 (6%) patients ≥75 years of age, received AMVUTTRA In HELIOS-B, a total of 299 (92%) patients ≥65 years old, including 203 (62%) ≥75 years old, received AMVUTTRA. No overall differences in safety or effectiveness were observed between these patients and younger patients.

8.6 Renal Impairment

No dose adjustment is recommended in patients with mild or moderate renal impairment (estimated glomerular filtration rate [eGFR] ≥30 to <90 mL/min/1.73 m^2) [see Clinical Pharmacology (12.3)]. AMVUTTRA has not been studied in patients with severe renal impairment or end-stage renal disease.

8.7 Hepatic Impairment

No dose adjustment is recommended in patients with mild (total bilirubin ≤1 × ULN and AST >1 × ULN, or total bilirubin >1.0 to 1.5 × ULN and any AST) or moderate (total bilirubin >1.5 to 3 × ULN and any AST) hepatic impairment [see Clinical Pharmacology (12.3)]. AMVUTTRA has not been studied in patients with severe hepatic impairment.

11 DESCRIPTION

AMVUTTRA contains vutrisiran, a chemically modified double-stranded small interfering ribonucleic acid (siRNA) that targets mutant and wild-type transthyretin (TTR) messenger RNA (mRNA) and is covalently linked to a ligand containing three N-acetylgalactosamine (GalNAc) residues to enable delivery of the siRNA to hepatocytes.

The structural formula of vutrisiran sodium is presented below.

Dashed lines denote Watson-Crick base pairing

The molecular formula of vutrisiran sodium is C530H672F9N171Na43O323P43S6 with a molecular weight of 17,290 Da. The molecular formula of the free acid is C530H715F9N171O323P43S6 with a molecular weight of 16,345 Da.

AMVUTTRA is supplied as a sterile, preservative-free, clear, colorless-to-yellow solution for subcutaneous injection. Each 0.5 mL of solution contains 25 mg of vutrisiran (equivalent to 26.5 mg vutrisiran sodium), 0.2 mg sodium phosphate monobasic dihydrate, 0.7 mg sodium phosphate dibasic dihydrate, 3.2 mg sodium chloride, water for injection, and sodium hydroxide and/or phosphoric acid to adjust the pH to ~7.

12 CLINICAL PHARMACOLOGY

12.1 Mechanism of Action

Vutrisiran is a double-stranded siRNA-GalNAc conjugate that causes degradation of mutant and wild-type TTR mRNA through RNA interference, which results in a reduction of serum TTR protein and TTR protein deposits in tissues.

12.2 Pharmacodynamics

The pharmacodynamic effects of AMVUTTRA were evaluated in patients with hATTR-PN and ATTR-CM, treated with 25 mg AMVUTTRA administered by subcutaneous injection once every 3 months.

Polyneuropathy of Hereditary Transthyretin-mediated Amyloidosis

In HELIOS-A [see Clinical Studies (14)], vutrisiran reduced mean serum TTR at steady state by 83%. Similar TTR reductions were observed regardless of Val30Met genotype status, weight, sex, age, or race.

Vutrisiran also reduced the mean steady state serum vitamin A by 62% over 9 months [see Warnings and Precautions (5.1)].

Cardiomyopathy of Wild-type (wt) or Hereditary Transthyretin-mediated Amyloidosis (hATTR)

In HELIOS-B, the mean serum TTR reduction profile was similar with that observed in HELIOS-A, and consistent across the subgroups studied (age, sex, race, body weight, anti-drug antibody [ADA] status, ATTR disease type (wtATTR versus hATTR), NYHA class, and baseline tafamidis use).

Vutrisiran reduced the mean steady state serum vitamin A by 65% over 36 months. [see Warnings and Precautions (5.1)].

Cardiac Biomarkers

Biomarkers associated with heart failure (NT-proBNP and Troponin I) favored AMVUTTRA over placebo.

Cardiac Electrophysiology

At a dose 12 times the recommended dosage of 25 mg once every three months, AMVUTTRA does not prolong the QT interval to any clinically relevant extent.

12.3 Pharmacokinetics

The pharmacokinetic (PK) properties of AMVUTTRA were evaluated following a single dose in healthy subjects and multiple doses in patients with hATTR amyloidosis, as summarized in Table 2.

Table 2: Pharmacokinetic Parameters of Vutrisiran
 |  | Vutrisiran
General Information
Dose Proportionality |  | Vutrisiran Cmax showed dose proportional increase while AUClast and AUCinf were slightly more than dose proportional following single subcutaneous doses ranging from 5 to 300 mg (i.e., 0.2 to 12 times the recommended dose)
Accumulation |  | No accumulation of vutrisiran was observed in plasma after repeated every 3 months dosage [After 25 mg every 3 months dosage in hATTR amyloidosis patients]
Absorption
Tmax [Median (Range)] |  | 4 (0.17, 12.0) hours [After 25 mg single dose in healthy subjects]
Distribution
Estimated Vd/F (%RSE) |  | 10.1 (5.8) L [Based on population PK model estimation]
Protein Binding |  | 80% [Vutrisiran plasma protein binding was concentration-dependent and decreased with increasing vutrisiran concentrations (from 78% at 0.5 mcg/mL to 19% at 50 mcg/mL)]
Organ Distribution |  | Vutrisiran distributes primarily to the liver after subcutaneous dosing
Elimination
Half-Life [Median (Range)] |  | 5.2 (2.2, 6.4) hours
Apparent Clearance [Median (Range)] |  | 21.4 (19.8, 30) L/hour
Metabolism
Primary Pathway |  | Vutrisiran is metabolized by endo- and exonucleases to short nucleotide fragments of varying sizes within the liver
Excretion
Primary Pathway |  | The mean fraction of unchanged vutrisiran eliminated in urine was approximately 19.4% at the recommended dose of 25 mg. The mean renal clearance of vutrisiran ranged from 4.5 to 5.7 L/hour [After single subcutaneous vutrisiran dose from 5 to 300 mg (i.e., 0.2 to 12 times the recommended dose) in healthy subjects]
AUCinf = area under the concentration-time curve from the time of dosing extrapolated to infinity; AUClast = area under the concentration-time curve from the time of dosing to the last measurable concentration; Cmax = maximum plasma concentration; CV = coefficient of variation; RSE = relative standard error; Tmax = time to maximum concentration; Vd/F = apparent volume of distribution

Specific Populations

No clinically significant differences in the pharmacokinetics of vutrisiran were observed based on age, sex, race, mild and moderate renal impairment (eGFR≥30 to <90 mL/min/1.73 m^2), or mild (total bilirubin ≤1 × ULN and AST >1 × ULN, or total bilirubin >1.0 to 1.5 × ULN and any AST) and moderate (total bilirubin >1.5 to 3 × ULN and any AST) hepatic impairment. Vutrisiran has not been studied in patients with severe renal impairment, end-stage renal disease, severe hepatic impairment, or in patients with prior liver transplant.

Drug Interaction Studies

No clinical drug-drug interaction studies have been performed with vutrisiran. In vitro studies suggest that vutrisiran is not a substrate or inhibitor of cytochrome P450 enzymes. Vutrisiran is not expected to cause drug-drug interactions by inducing CYP enzymes or modulating the activities of drug transporters.

12.6 Immunogenicity

The observed incidence of anti-drug antibody (ADA, including neutralizing antibody) is highly dependent on the sensitivity and specificity of the assay. Differences in assay methods preclude meaningful comparisons of the incidence of ADA in the studies described below with the incidence of ADA in the other studies, including those of AMVUTTRA or of other siRNA products.

In HELIOS-A and HELIOS-B studies, 3 (2.5%) and 1 (0.3%) patient treated with AMVUTTRA, respectively, developed transient, low titer anti-drug antibodies. The available data are limited to make definitive conclusions regarding the effect of anti-drug antibodies on pharmacokinetics or pharmacodynamics of AMVUTTRA.

13 NONCLINICAL TOXICOLOGY

13.1 Carcinogenesis, Mutagenesis, Impairment of Fertility

Carcinogenesis

Subcutaneous administration of vutrisiran to male mice (0, 2, 6, or 13 mg/kg once every 4 weeks) for 100 weeks and to female mice (0, 3, 9, or 18 mg/kg once every 4 weeks) for 98 weeks resulted in no increase in tumors.

Subcutaneous administration of vutrisiran to male rats (0, 4, 7.5, or 15 mg/kg once every 4 weeks or 15 mg/kg once every 12 weeks) for 99 weeks and to female rats (0, 6, 12.5, or 25 mg/kg once every 4 weeks or 25 mg/kg once every 12 weeks) for 86-87 weeks resulted in no increase in tumors.

Mutagenesis

Vutrisiran was negative for mutagenicity in in vitro (bacterial mutagenicity, chromosomal aberration in human blood peripheral lymphocytes) and in vivo (rat bone marrow micronucleus) assays.

Impairment of Fertility

Subcutaneous administration of vutrisiran (0, 15, 30, or 70 mg/kg/week) to male and female rats prior to and during mating and continuing in females to gestation day 6 resulted in no adverse effects on fertility or reproductive performance.

14 CLINICAL STUDIES

14.1 Polyneuropathy of Hereditary Transthyretin-mediated Amyloidosis

The efficacy of AMVUTTRA was evaluated in a randomized, open-label clinical trial in adult patients with hATTR-PN (HELIOS-A; NCT03759379). Patients were randomized 3:1 to receive 25 mg of AMVUTTRA subcutaneously once every 3 months (N=122), or 0.3 mg/kg patisiran intravenously every 3 weeks (N=42) as a reference group. Ninety-seven percent of AMVUTTRA-treated patients and 93% of patisiran-treated patients completed at least 9 months of the assigned treatment.

Efficacy assessments were based on a comparison of the AMVUTTRA arm of HELIOS-A with an external placebo group in another study (NCT01960348) composed of a comparable population of adult patients with polyneuropathy caused by hATTR amyloidosis.

The primary efficacy endpoint was the change from baseline to Month 9 in modified Neuropathy Impairment Score +7 (mNIS+7). The mNIS+7 is an objective assessment of neuropathy and comprises the NIS and Modified +7 composite scores. In the version of the mNIS+7 used in the trial, the NIS objectively measures deficits in cranial nerve function, muscle strength, and reflexes, and the +7 assesses postural blood pressure, quantitative sensory testing, and peripheral nerve electrophysiology. The mNIS+7 has a total score range from 0 to 304 points, with higher scores representing a greater severity of disease.

The clinical meaningfulness of effects on the mNIS+7 was assessed by the change from baseline to Month 9 in Norfolk Quality of Life-Diabetic Neuropathy (QoL-DN) total score. The Norfolk QoL-DN scale is a patient-reported assessment that evaluates the subjective experience of neuropathy in the following domains: physical functioning/large fiber neuropathy, activities of daily living, symptoms, small fiber neuropathy, and autonomic neuropathy. The Norfolk QoL-DN has a total score range from -4 to 136, with higher scores representing greater impairment.

Additional endpoints were gait speed, as measured by the 10-meter walk test (10MWT), and modified body mass index (mBMI).

Treatment with AMVUTTRA in HELIOS-A resulted in statistically significant improvements in the mNIS+7, Norfolk QoL-DN total score, and 10-meter walk test at Month 9 compared to placebo in the external study (p<0.001) [Table 3, Figure 1, and Figure 3]. The distributions of changes in mNIS+7 and Norfolk QoL-DN total scores from baseline to Month 9 by percent of patients are shown in Figure 2 and Figure 4, respectively.

The change from baseline to Month 9 in modified body mass index nominally favored AMVUTTRA [Table 3].

Table 3: Clinical Efficacy Results (Comparison of AMVUTTRA Treatment in HELIOS-A to an External Placebo Control [External placebo group from another randomized controlled trial (NCT01960348)])
Endpoint [All endpoints analyzed using the analysis of covariance (ANCOVA) with multiple imputation (MI) method)] | Baseline, Mean (SD) |  | Change from Baseline to Month 9, LS Mean (SEM) |  | AMVUTTRA-Placebo Treatment Difference, LS Mean (95% CI) | p-value
Endpoint [All endpoints analyzed using the analysis of covariance (ANCOVA) with multiple imputation (MI) method)] | AMVUTTRA N=122 (HELIOS-A) | Placebo N=77 (NCT01960348) | AMVUTTRA (HELIOS-A) | Placebo (NCT01960348) | AMVUTTRA-Placebo Treatment Difference, LS Mean (95% CI) | p-value
mNIS+7 [A lower number indicates less impairment/fewer symptoms] | 60.6 (36.0) | 74.6 (37.0) | -2.2 (1.4) | 14.8 (2.0) | -17.0 (-21.8, -12.2) | p<0.001
Norfolk QoL-DN | 47.1 (26.3) | 55.5 (24.3) | -3.3 (1.7) | 12.9 (2.2) | -16.2 (-21.7, -10.8) | p<0.001
10-meter walk test (m/sec) [A higher number indicates less disability/less impairment] | 1.01 (0.39) | 0.79 (0.32) | 0 (0.02) | -0.13 (0.03) | 0.13 (0.07, 0.19) | p<0.001
mBMI [mBMI: nominal p-value; body mass index (BMI; kg/m^2) multiplied by serum albumin (g/L).] | 1058 (234) | 990 (214) | 7.6 (7.9) | -60.2 (10.1) | 67.8 (43.0, 92.6) | p<0.001
CI = confidence interval; LS mean = least squares mean; mBMI = modified body mass index; mNIS = modified Neuropathy Impairment Score; QoL-DN = Quality of Life-Diabetic Neuropathy; SD = standard deviation; SEM = standard error of the mean

Figure 1: Change from Baseline in mNIS+7
(Comparison of AMVUTTRA Treatment in HELIOS-A to an External Placebo Control [External placebo group from another randomized controlled trial (NCT01960348)])

A decrease in mNIS+7 indicates improvement
Δ indicates between-group treatment difference, shown as the LS mean difference (95% CI) for AMVUTTRA – placebo

Figure 2: Histogram of mNIS+7 Change from Baseline at Month 9
(Comparison of AMVUTTRA Treatment in HELIOS-A to an External Placebo Control [External placebo group from another randomized controlled trial (NCT01960348)])

Categories are mutually exclusive; patients who died before 9 months are summarized in the "Death" category only

Figure 3: Change from Baseline in Norfolk QoL-DN Total Score
(Comparison of AMVUTTRA Treatment in HELIOS-A to an External Placebo Control [External placebo group from another randomized controlled trial (NCT01960348)])

A decrease in Norfolk QoL-DN score indicates improvement
Δ indicates between-group treatment difference, shown as the LS mean difference (95% CI) for AMVUTTRA – placebo

Figure 4: Histogram of Norfolk QoL-DN Total Score Change from Baseline at Month 9
(Comparison of AMVUTTRA Treatment in HELIOS-A to an External Placebo Control [External placebo group from another randomized controlled trial (NCT01960348)])

Categories are mutually exclusive; patients who died before 9 months are summarized in the "Death" category only

Patients receiving AMVUTTRA in HELIOS-A experienced similar improvements relative to those in the external placebo group in mNIS+7 and Norfolk QoL-DN total score across all subgroups including age, sex, race, region, NIS score, Val30Met genotype status, and disease stage.

14.2 Cardiomyopathy of Wild-type or Hereditary Transthyretin-mediated Amyloidosis

The efficacy of AMVUTTRA was evaluated in a multicenter, international, randomized, double-blind, placebo-controlled trial (HELIOS-B, NCT04153149) in 654 adult patients with wild-type or hereditary ATTR-CM. Patients were randomized 1:1 to receive 25 mg of AMVUTTRA (n=326) subcutaneously once every 3 months, or matching placebo (n=328).

Treatment assignment was stratified by baseline tafamidis use (yes versus no), ATTR disease type (wtATTR or hATTR amyloidosis), and by baseline New York Heart Association (NYHA) Class I or II and age <75 years versus all other. At baseline, 40% of patients were on tafamidis. The mean age of study participants was 75 years, 93% were male, 84% were White, 7% were Black or African American, 6% were Asian, 2% did not report race and 1% were race other, 88% had wild-type ATTR, 13% were NYHA Class I, 78% were NYHA Class II, and 9% NYHA Class III. No significant imbalance in baseline characteristics was observed between the two treatment groups.

Participants were permitted to initiate open-label tafamidis during the study. A total of 85 participants initiated tafamidis: 44 (22%) in the AMVUTTRA arm and 41 (21%) in the placebo arm. The median time to initiation of tafamidis for these 85 participants was 18 months.

The primary efficacy endpoint was the composite outcome of all-cause mortality and recurrent CV events (CV hospitalizations and urgent heart failure [UHF] visits) during the double-blind treatment period of up to 36 months, evaluated in the overall population and in the monotherapy population (defined as patients not receiving tafamidis at study baseline).

AMVUTTRA led to significant reduction in the risk of all-cause mortality and recurrent CV events compared to placebo in the overall and monotherapy population of 28% and 33%, respectively (Table 4). The majority of the deaths (77%) were CV-related. A Kaplan-Meier curve illustrating time to first CV event or all-cause mortality is presented in Figure 5.

Both components of the primary composite endpoint individually contributed to the treatment effect in the overall and monotherapy population (Table 4).

Table 4: Primary Composite Endpoint and its Individual Components in HELIOS-B
Endpoint |  | Overall population |  | Monotherapy population
Endpoint |  | AMVUTTRA (N=326) | Placebo (N=328) | AMVUTTRA (N=196) | Placebo (N=199)
Primary composite endpoint [Primary composite endpoint defined as: composite outcome of all-cause mortality and recurrent CV events. Primary analysis included at least 33 months (and up to 36 months) follow-up on all patients.] | Hazard Ratio (95% CI) [Hazard Ratio (95% CI) and p-value are based on a modified Andersen-Gill model.] p-value | 0.72 (0.55, 0.93) 0.01 |  | 0.67 (0.49, 0.93) 0.02
Components of the Primary Composite Endpoint
All-cause mortality | Hazard Ratio (95% CI) [Hazard Ratio (95% CI) is based on a Cox proportional hazard model.] | 0.69 (0.49, 0.98) |  | 0.71 (0.47, 1.06)
CV hospitalizations and UHF visits | Hazard Ratio (95% CI) | 0.73 (0.55, 0.96) |  | 0.67 (0.47, 0.96)
Abbreviations: CI=confidence interval; CV=cardiovascular; UHF=urgent heart failure.
Heart transplantation and left ventricular assist device placement are treated as death. Deaths after study discontinuation are included in the all-cause mortality component analysis.

Figure 5: Time to All-Cause Mortality or First CV Event (Overall population)

Abbreviations: CI=confidence interval; CV=cardiovascular; HR = hazard ratio.
Heart transplantation and left ventricular assist device placement are treated as death. HR and 95% CI are based on a Cox proportional hazard model. First CV event = First CV hospitalization or urgent heart failure visit after randomization.

Results from the subgroup analysis for the primary composite endpoint were consistent across prespecified subgroups in the overall population (Figure 6) and monotherapy population.

Figure 6: Subgroup Analyses of the Primary Composite Endpoint (Overall Population)

Abbreviations: ATTR = transthyretin amyloidosis; CI = confidence interval; hATTR = hereditary transthyretin amyloidosis; HR = hazard ratio; NT-pro-BNP = N-terminal prohormone of B-type natriuretic peptide; NYHA = New York Heart Association; wtATTR = wild-type transthyretin amyloidosis.
HR and 95% CI are based on modified Andersen-Gill model analyses.

The treatment effect of AMVUTTRA on functional capacity and health status were assessed by the change from baseline to Month 30 in distance walked on 6-Minute Walk Test (6-MWT), and the Kansas City Cardiomyopathy Questionnaire-Overall Summary (KCCQ-OS) score, respectively.

At Month 30, the LS mean difference in change from baseline in distance walked on 6-MWT was 22 (95% CI: 8, 35; p=0.002) meters and 25 (95% CI: 7, 44; p=0.006) meters favoring AMVUTTRA over placebo in the overall population and monotherapy population, respectively.

At Month 30, the LS mean difference in the change from baseline in KCCQ-OS was 6 (95% CI: 2, 9; p=0.001) and 8 (95% CI: 4, 13; p=0.0003) favoring AMVUTTRA over placebo in the overall population and monotherapy population respectively.

16 HOW SUPPLIED/STORAGE AND HANDLING

16.1 How Supplied

AMVUTTRA is a sterile, preservative-free, clear, colorless-to-yellow solution for subcutaneous injection. AMVUTTRA is supplied as 25 mg/0.5 mL solution in a single-dose 1-mL prefilled syringe made from Type I glass with stainless steel 29-gauge needle with a needle shield. The prefilled syringe components are not made with natural rubber latex.

AMVUTTRA is available in cartons containing one single-dose prefilled syringe each.

The NDC is: 71336-1003-1.

16.2 Storage and Handling

Store at 2°C to 30°C (36°F to 86°F) in the original carton, until ready for use. Do not freeze.

17 PATIENT COUNSELING INFORMATION

Recommended Vitamin A Supplementation

Inform patients that AMVUTTRA treatment leads to a decrease in serum vitamin A levels. Instruct patients to take the recommended daily allowance of vitamin A. Advise patients to contact their healthcare provider if they experience ocular symptoms suggestive of vitamin A deficiency (e.g., night blindness) and refer them to an ophthalmologist if they develop these symptoms [see Warnings and Precautions (5.1)].

Pregnancy

Instruct patients that if they are pregnant or plan to become pregnant while taking AMVUTTRA they should inform their healthcare provider. Inform patients of the potential risk to the fetus, including that AMVUTTRA treatment leads to a decrease in serum vitamin A levels [see Use in Specific Populations (8.1) and Clinical Pharmacology (12.2)].

Manufactured for: Alnylam Pharmaceuticals, Inc., Cambridge, MA 02142
AMVUTTRA is a registered trademark of Alnylam Pharmaceuticals, Inc.

PRINCIPAL DISPLAY PANEL - 25 mg/0.5 mL Syringe Carton

NDC 71336-1003-1

amvuttra ™
(vutrisiran) injection

25 mg/0.5 mL

For Subcutaneous Injection by
Healthcare Professional Only

Rx Only

Do not use if
seal is broken

1 x 25 mg single-dose
prefilled syringe